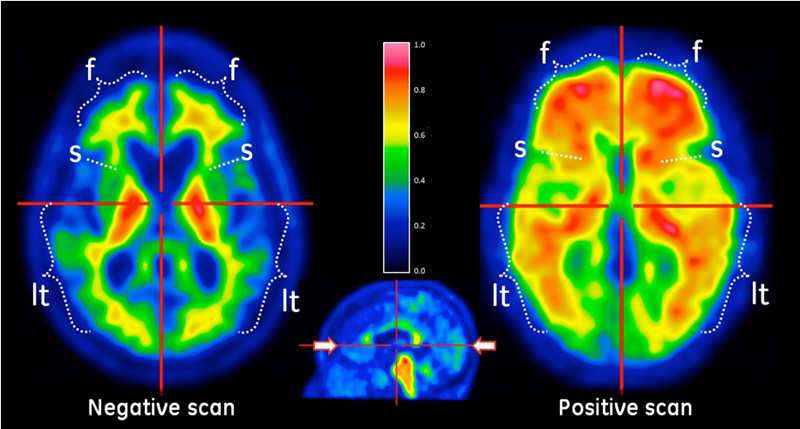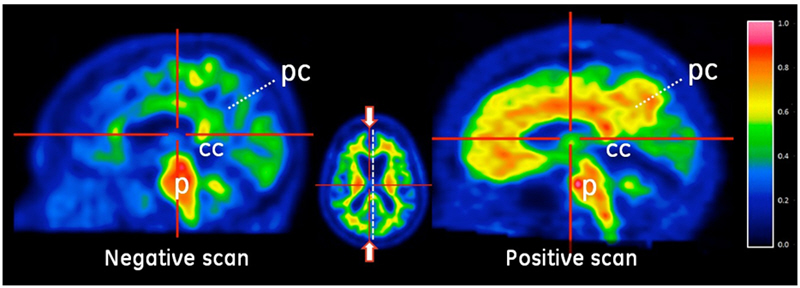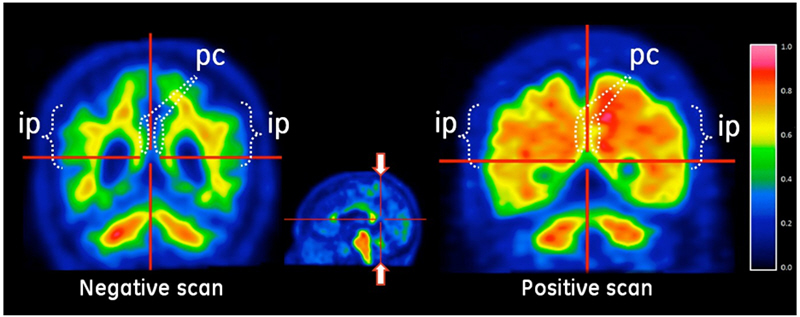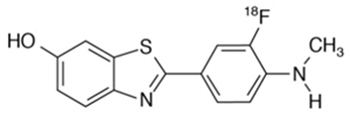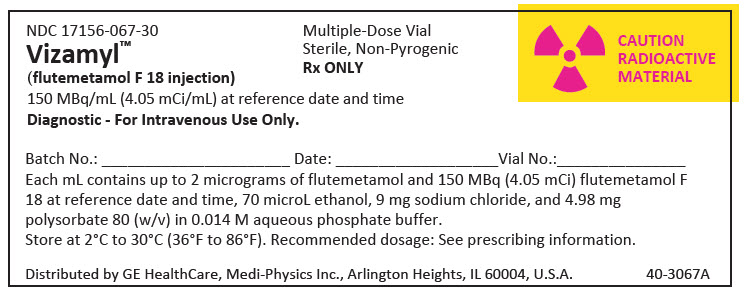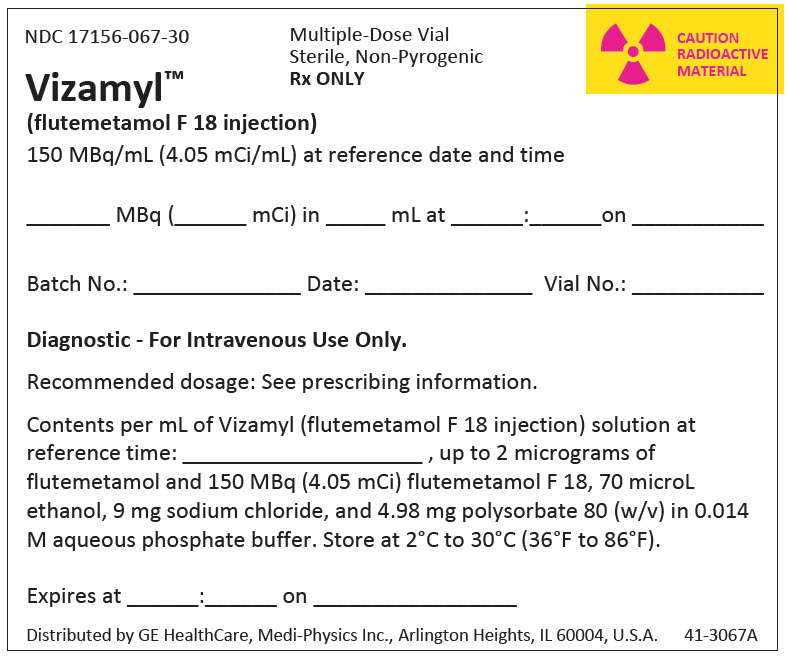 DRUG LABEL: Vizamyl
NDC: 17156-067 | Form: SOLUTION
Manufacturer: GE Healthcare Inc. (Medi-Physics, Inc. dba GE Healthcare)
Category: prescription | Type: HUMAN PRESCRIPTION DRUG LABEL
Date: 20251120

ACTIVE INGREDIENTS: FLUTEMETAMOL F-18 4.05 mCi/1 mL
INACTIVE INGREDIENTS: ALCOHOL 70 uL/1 mL; SODIUM CHLORIDE; POLYSORBATE 80

HIGHLIGHTS OF PRESCRIBING INFORMATION

These highlights do not include all the information needed to use VIZAMYL safely and effectively. See full prescribing information for VIZAMYL.
VIZAMYL™ (flutemetamol F 18 injection), for intravenous use
Initial U.S. Approval: 2013

RECENT MAJOR CHANGES

Indications and Usage (1) | 6/2025
Dosage and Administration, Image Interpretation (2.5) | 6/2025
Warnings and Precautions, Anaphylaxis and Other Serious Hypersensitivity Reactions (5.1) | 6/2025

1 INDICATIONS AND USAGE

VIZAMYL is a radioactive diagnostic drug indicated for positron emission tomography (PET) of the brain to estimate amyloid beta neuritic plaque density in adults with cognitive impairment for:

- Evaluation of Alzheimer's disease (AD) and other causes of cognitive decline
- Selection of patients who are indicated for amyloid beta-directed therapy as described in the prescribing information of the therapeutic products (1)

2 DOSAGE AND ADMINISTRATION

- The recommended amount of radioactivity is 185 MBq (5 mCi) administered as a single intravenous bolus within 40 seconds in a total volume of up to 10 mL. (2.2)
- Follow injection with an intravenous flush of 5 mL to 15 mL of 0.9% sodium chloride injection. (2.2)
- Obtain 10-minute to 20-minute PET images starting approximately 60 minutes to 120 minutes after drug administration. (2.3)
- See full prescribing information for image interpretation and radiation dosimetry. (2.4, 2.5, 2.6)

3 DOSAGE FORMS AND STRENGTHS

Injection: 150 MBq/mL (4.05 mCi/mL) of flutemetamol F 18 in up to 30 mL volume at reference date and time in a multiple-dose vial (3)

4 CONTRAINDICATIONS

Known hypersensitivity to VIZAMYL or polysorbate 80 (4)

5 WARNINGS AND PRECAUTIONS

- Anaphylaxis and Other Serious Hypersensitivity Reactions: Always have emergency resuscitation equipment and trained personnel available at the time of VIZAMYL administration. (5.1)
- Risk of Image Misinterpretation and Other Errors: Image interpretation errors have been observed. (5.2)
- Radiation Risk: VIZAMYL contributes to a patient's long-term cumulative radiation exposure. Ensure safe drug handling to protect patients and health care providers from unintentional radiation exposure. Advise patients to hydrate before and after administration and to void frequently after administration. (2.1, 2.2, 5.3)

6 ADVERSE REACTIONS

Most common adverse reactions (incidence ≥ 1%) were flushing, increased blood pressure, headache, nausea, and dizziness. (6.1)

To report SUSPECTED ADVERSE REACTIONS, contact GE HealthCare at 1-800-654-0118 or FDA at 1-800-FDA-1088 or www.fda.gov/medwatch.

8 USE IN SPECIFIC POPULATIONS

Lactation: Temporarily discontinue breastfeeding. A lactating woman should pump and discard breast milk for 24 hours after VIZAMYL administration. (8.2)

FULL PRESCRIBING INFORMATION

1 INDICATIONS AND USAGE

VIZAMYL is indicated for positron emission tomography (PET) of the brain to estimate amyloid beta neuritic plaque density in adults with cognitive impairment for:

- Evaluation of Alzheimer's disease (AD) and other causes of cognitive decline
- Selection of patients who are indicated for amyloid beta-directed therapy as described in the prescribing information of the therapeutic products

2 DOSAGE AND ADMINISTRATION

2.1 Radiation Safety - Drug Handling

Handle VIZAMYL with appropriate safety measures to minimize radiation exposure during administration [see Warnings and Precautions (5.3)]. Use waterproof gloves and effective radiation shielding, including lead-glass syringe shields when handling and administering VIZAMYL.

Radiopharmaceuticals, including VIZAMYL, should be used by or under the control of healthcare providers who are qualified by specific training and experience in the safe use and handling of radionuclides, and whose experience and training have been approved by the appropriate governmental agency authorized to license the use of radionuclides.

2.2 Recommended Dosage and Administration Instructions

Recommended Dosage

The recommended amount of activity of VIZAMYL is 185 MBq (5 mCi) in a total volume of up to 10 mL, administered as a single intravenous bolus within 40 seconds. The maximum mass dose is 20 mcg. Follow the injection with an intravenous flush of 5 mL to 15 mL of 0.9% sodium chloride injection.

Patient Preparation

Instruct patients to hydrate before and after VIZAMYL administration and to void frequently following VIZAMYL administration to reduce radiation exposure [see Warnings and Precautions (5.3)].

Administration

- Use aseptic technique and radiation shielding to withdraw and administer VIZAMYL.
- Visually inspect VIZAMYL for particulate matter and discoloration prior to administration. Do not use VIZAMYL if it contains particulate matter or if it is discolored.
- Do not dilute VIZAMYL.
- Calculate the necessary volume to administer based on calibration time and required dose.
- Measure the activity of VIZAMYL with a dose calibrator immediately prior to administration to the patient.
- Dispose of unused product in a safe manner in compliance with applicable regulations.

2.3 Image Acquisition Instructions

- Position the patient supine with the head positioned to center the brain, including the cerebellum, within a single field of view. The patient's head should be tilted so that the anterior commissure-posterior commissure (AC-PC) plane is at right angles to the bore-axis of the PET scanner, with the head positioned in a suitable head support. Tape or other flexible head restraints may be employed to reduce head movement.
- Acquire 10-minute to 20-minute PET images starting 60 minutes to 120 minutes after VIZAMYL administration using a PET scanner in 3-D mode with appropriate data corrections.
- Iterative or filtered back-projection reconstruction is recommended with a slice thickness of 2 mm to 4 mm, and matrix size of 128 × 128 with pixel sizes of approximately 2 mm. Where a post-smoothing filter is applied, full width at half maximum (FWHM) of not more than 5 mm is recommended; filter FWHM should be chosen to optimize the signal-to-noise ratio while preserving the sharpness of the reconstructed image.

2.4 Image Orientation and Display

Image Orientation

Orient axial and coronal images to show symmetry of brain structures, with equal heights of structures bilaterally. Orient sagittal images so that the head and neck are neither flexed nor extended; the anterior and posterior aspects of the corpus callosum should be parallel to the AC-PC line as shown in Figure 2.

Image Display

- Display images with all planes (axial, sagittal, and coronal planes) linked by crosshairs.
- Select a color scale that provides a progression of low through high intensity (e.g., rainbow or Sokoloff). The selected color scale should: (1) provide colors that allow the reader to discriminate signal intensity above and below the signal intensity of the pons; (2) provide a color for regions with little or no amyloid binding such as the cerebellar cortex; and (3) provide a range of at least five distinct colors above 50% to 60% of the peak signal intensity.
- Display the reference scale. Adjust the color scale to set the pons to approximately 90% maximum signal intensity. The cerebellar cortex should represent approximately 20% to 30% of peak signal intensity on both negative and positive VIZAMYL scans.
- Display axial brain slices sequentially from the bottom of the brain to the top and look for signs of atrophy.
- Systematically review signal intensity in the following brain regions (recommended plane) for image interpretation [see Dosage and Administration (2.5)]:
  - Frontal lobes (axial, with optional sagittal plane view)
  - Posterior cingulate and precuneus (sagittal, with optional coronal plane view)
  - Lateral temporal lobes (axial, with optional coronal plane view)
  - Inferolateral parietal lobes (coronal, with optional axial plane view)
  - Striatum (axial, with optional sagittal plane view)

2.5 Image Interpretation

Visual Assessment

VIZAMYL images should be interpreted only by readers who successfully complete the training program provided by the manufacturer [see Warnings and Precautions (5.2)].

Perform image interpretation independently of the patient's clinical features, relying on the recognition of unique image features.

Interpret VIZAMYL images based upon the distribution of signal intensity within the cerebral cortex by comparing the signal intensity in the cortical gray matter and the adjacent white matter, or based on the signal intensity in the five regions mentioned above [see Dosage and Administration (2.4)]. The signal intensity in the cerebellum does not contribute to scan interpretation. For example, a positive scan may show retained cerebellar gray-white contrast even when the cortical gray-white contrast is lost. Among patients with clinically important amyloid beta neuritic plaques in the brain, the temporal lobes, parietal lobes, and striatum may not be as affected compared to other brain regions. Therefore, in some images, the signal in these regions may not be as intense as in the frontal lobes or the posterior cingulate and precuneus regions.

Some scans may be difficult to interpret due to image noise, suboptimal patient positioning, or over-smoothing of the reconstructed image. Atrophy may affect the interpretability of scans, particularly in the frontal, temporal, and parietal lobes. Other factors that may affect the ability to interpret VIZAMYL images include patient factors such as brain pathology, surgical changes, post-radiation therapy changes, and implants. For cases in which atrophy is apparent or suspected and there is uncertainty as to the location of the gray matter on the PET scan, examine the striatum for VIZAMYL signal as it is less affected by atrophy than other regions of the brain. If the patient's MRI or CT brain images are available, examine the CT or MRI images to clarify the relationship between VIZAMYL signal and gray matter anatomy [see Warnings and Precautions (5.2)].

Negative VIZAMYL Scan

Negative scans show more signal in white matter than in gray matter, creating clear gray-white matter contrast.

Specifically, a negative scan would have the following characteristics:

frontal, lateral temporal, and inferolateral parietal lobes: gradual gradient from bright intensity of the white matter to lower intensity at the periphery of the brain; distinct sulci with concave surfaces (white matter sulcal pattern),
and
posterior cingulate and precuneus: gray matter uptake below 50% to 60% of peak intensity; gap of lower intensity separates two hemispheres on coronal view,
and
striatum: approximately 50% of peak intensity or lower in the region between the higher intensities of the thalamus and frontal white matter (striatal "gap").

A negative scan indicates sparse to no neuritic plaques. In patients being evaluated for AD and other causes of cognitive decline who have not been treated with amyloid beta-directed therapy, a negative scan is inconsistent with a neuropathological diagnosis of AD at the time of image acquisition and reduces the likelihood that a patient's cognitive impairment is due to AD. A negative scan result does not preclude the accumulation of amyloid beta in the brain in the future.

Positive VIZAMYL Scan

Positive scans show at least one cortical region with reduction or loss of the normally distinct gray-white matter contrast. These scans have one or more regions with increased cortical gray matter signal (above 50% to 60% peak intensity) and/or reduced (or absent) gray-white matter contrast (white matter sulcal pattern is less distinct). A positive scan may have one or more regions in which gray matter signal is as intense or exceeds the intensity in adjacent white matter.

Specifically, a positive scan would have the following characteristics:

frontal, lateral temporal, or inferolateral parietal lobes: high intensity seen to the periphery of the brain, with sharp reduction of intensity at the brain margin; sulci may not be distinct due to fill-in by high intensity gray matter resulting in a convex appearance of the surface at the edge of the brain,
or
posterior cingulate and precuneus: gray matter uptake above 50% to 60% of peak intensity; high gray matter intensity that closes the gap between the two hemispheres on coronal view,
or
striatum: intensity above 50% to 60% of peak intensity; gap between thalamus and frontal white matter not distinct.

If any one of the brain regions systematically reviewed for signal intensity is positive in either hemisphere, then the scan is considered positive [see Dosage and Administration (2.4)]. Otherwise, the scan is considered negative.

A positive scan establishes the presence of moderate to frequent neuritic plaques. Neuropathological examination has shown that moderate to frequent amyloid beta neuritic plaques are present in patients with AD, but may also be present in patients with other types of neurologic conditions as well as older people with normal cognition.

Figures 1, 2, and 3 provide examples of negative and positive scans.

Figure 1: Axial View of Negative (left) and Positive (right) VIZAMYL Scans. The axial slices that cut through the frontal pole and inferior aspect of the splenium are shown using a rainbow color scale. The left image shows a white matter sulcal pattern at the frontal (f) and lateral temporal (lt) regions with a color intensity that tapers to the periphery, as well as less signal intensity in the striatal region(s). The right image shows absence of the white matter sulcal pattern with intensity radiating to a sharply defined convex edge, as well as more signal intensity in the striatum. In both the frontal and lateral temporal regions, the intensity is higher in the gray matter regions of the right image compared to those of the left image.

Figure 2: Sagittal View of Negative (left) and Positive (right) VIZAMYL Scans. The sagittal slices are slightly off midline in one hemisphere and shown using a rainbow color scale. In the posterior cingulate (pc) region, which is superior and posterior to the corpus callosum (cc), the left image shows signal intensity below 50% of peak intensity whereas the right image shows intensity above 60% of peak intensity. The pons (p) is set to approximately 90% of the maximum intensity.

Figure 3: Coronal View of Negative (left) and Positive (right) VIZAMYL Scans. The coronal slices are located posterior to the corpus callosum. The left image shows a white matter sulcal pattern in the inferior parietal (ip) regions that is not evident in the right image. Relative to the left image, the right image shows increased signal intensity in the posterior cinguli (pc) and increased radial extent of high intensity to the lateral surfaces of the parietal lobes particularly evident in the inferior parietal regions.

Quantitative Analysis

Quantification of amyloid beta neuritic plaque levels (e.g., Centiloid scale or standardized uptake value ratio (SUVR)) can be used in conjunction with visual assessment and performed with FDA-authorized software indicated for quantification of brain amyloid PET scans. Refer to the drug manufacturer's training materials for qualitative and quantitative assessment and to the software manufacturers' documentation for software operation.

2.6 Radiation Dosimetry

Estimated radiation absorbed doses for adults following intravenous injection of VIZAMYL are shown in Table 1.

Values were calculated from human biodistribution data using OLINDA/EXM software and assuming emptying of the urinary bladder at 3.5-hour intervals.

The whole-body effective dose resulting from administration of 185 MBq (5 mCi) of VIZAMYL to an adult is estimated to be 5.9 mSv. When PET/CT is performed, exposure to radiation will increase by an amount dependent on the settings used in the CT acquisition.

Table 1: Estimated Radiation Absorbed Doses in Organs/Tissues in Adults Who Received VIZAMYL
Organ/Tissue | Absorbed Dose Per Unit Administered Activity (microGy/MBq)
Adrenals | 13
Brain | 11
Breasts | 5
Gallbladder wall | 287
Heart wall | 14
Kidneys | 31
Liver | 57
Lower large intestine wall | 42
Lungs | 16
Muscle | 9
Osteogenic cells | 11
Ovaries | 25
Pancreas | 15
Red marrow | 13
Skin | 5
Small intestine wall | 102
Spleen | 15
Stomach wall | 12
Testes | 8
Thymus | 6
Thyroid | 6
Upper large intestine wall | 117
Urinary bladder wall | 145
Uterus | 25
Total body | 12
Effective Dose | 32 (microSv/MBq)

3 DOSAGE FORMS AND STRENGTHS

Injection: 150 MBq/mL (4.05 mCi/mL) of flutemetamol F 18 in up to 30 mL volume at reference date and time as a clear, colorless to slightly yellow solution in a multiple-dose vial.

4 CONTRAINDICATIONS

VIZAMYL is contraindicated in patients with a history of hypersensitivity reaction to VIZAMYL or polysorbate 80 [see Warnings and Precautions (5.1)].

5 WARNINGS AND PRECAUTIONS

5.1 Anaphylaxis and Other Serious Hypersensitivity Reactions

Serious hypersensitivity reactions including anaphylaxis, presenting with flushing, dyspnea, and hypotension, have been observed within minutes following VIZAMYL administration. These reactions may occur in patients with no history of exposure to VIZAMYL [see Adverse Reactions (6.1, 6.2)].

Obtain a history of allergy or hypersensitivity reactions. Always have resuscitation equipment and trained personnel immediately available at the time of VIZAMYL administration. If a hypersensitivity reaction is suspected, immediately discontinue the injection and initiate appropriate therapy. VIZAMYL is contraindicated in patients with a history of hypersensitivity to VIZAMYL or polysorbate 80 [see Contraindications (4)].

5.2 Risk of Image Misinterpretation and Other Errors

Errors may occur in the estimation of amyloid beta neuritic plaque density during VIZAMYL image interpretation [see Clinical Studies (14)].

The use of clinical information in the interpretation of VIZAMYL images has not been evaluated and may lead to an inaccurate assessment. Extensive brain atrophy and motion artifacts that distort the image may limit the ability to distinguish gray and white matter on a VIZAMYL scan.

Perform image interpretation independently of the patient's clinical information. For cases where there is uncertainty as to the location of cortical signal, use co-registered anatomical imaging to improve localization of signal or examine the striatum for VIZAMYL signal as it is less affected by atrophy [see Dosage and Administration (2.5)].

5.3 Radiation Risk

VIZAMYL contributes to a patient's overall long-term cumulative radiation exposure. Long-term cumulative radiation exposure is associated with an increased risk of cancer. Ensure safe drug handling to protect patients and health care providers from unintentional radiation exposure. Advise patients to hydrate before and after administration and to void frequently after administration [see Dosage and Administration (2.1, 2.2)].

6 ADVERSE REACTIONS

The following clinically significant adverse reaction is described elsewhere in the labeling:

- Hypersensitivity Reactions [see Warnings and Precautions (5.1)]

6.1 Clinical Trials Experience

Because clinical trials are conducted under widely varying conditions, adverse reaction rates observed in the clinical trials of a drug cannot be directly compared to rates in the clinical trials of another drug and may not reflect the rates observed in clinical practice.

The safety of VIZAMYL was evaluated in 761 adult subjects who received VIZAMYL by intravenous injection in clinical trials. Most subjects (70%) received a dose of 185 MBq (5 mCi). The subjects had a mean age of 62 years (range 18 years to 93 years); 45% of the subjects were male and 91% were White.

A serious hypersensitivity reaction characterized by flushing, dyspnea, and chest pressure was reported within minutes following VIZAMYL administration in one subject who recovered with treatment.

Adverse reactions reported in ≥ 1% of subjects from the clinical trials are shown in Table 2.

Table 2: Adverse Reactions Reported in ≥ 1% of Adult Subjects Who Received VIZAMYL in Clinical Trials
Adverse Reaction | VIZAMYL N=761 %
Flushing | 2
Increased blood pressure | 2
Headache | 1
Nausea | 1
Dizziness | 1

6.2 Postmarketing Experience

The following adverse reactions have been identified during postapproval use of VIZAMYL. Because these reactions are reported voluntarily from a population of uncertain size, it is not always possible to reliably estimate their frequency or establish a causal relationship to drug exposure.

Immune system disorders: anaphylactic reactions

8 USE IN SPECIFIC POPULATIONS

8.1 Pregnancy

Risk Summary

There are no available data on VIZAMYL use in pregnant women to evaluate for a drug-associated risk of major birth defects, miscarriage, or adverse maternal or fetal outcomes. Animal reproduction studies have not been conducted with flutemetamol F 18 to evaluate its effect on female reproduction and embryo-fetal development.

All radiopharmaceuticals, including VIZAMYL, have the potential to cause fetal harm depending on the stage of fetal development and the magnitude of the radiation dose. If considering VIZAMYL administration to a pregnant woman, inform the patient about the potential for adverse pregnancy outcomes based on the radiation dose from the drug and the gestational timing of exposure.

The background risk of major birth defects and miscarriage for the indicated population is unknown. All pregnancies have a background risk of birth defect, loss, or other adverse outcomes. In the U.S. general population, the estimated background risk of major birth defects and miscarriage in clinically recognized pregnancies is 2% to 4% and 15% to 20%, respectively.

8.2 Lactation

Risk Summary

There are no data on the presence of flutemetamol F 18 or metabolites in human milk or its effects on the breastfed infant or milk production. Exposure of VIZAMYL to a breastfed infant can be minimized by temporary discontinuation of breastfeeding (see Clinical Considerations). The developmental and health benefits of breastfeeding should be considered along with the mother's clinical need for VIZAMYL and any potential adverse effects on the breastfed child from VIZAMYL or from the underlying maternal condition.

Clinical Considerations

To decrease radiation exposure to the breastfed infant, advise a lactating woman to interrupt breastfeeding, and pump and discard breast milk for 24 hours after administration of VIZAMYL.

8.4 Pediatric Use

The safety and effectiveness of VIZAMYL have not been established in pediatric patients.

8.5 Geriatric Use

Of the 761 subjects in clinical studies of VIZAMYL, 447 (59%) subjects were 65 years of age and older, while 246 (32%) subjects were 75 years of age and older. No overall differences in safety or effectiveness were observed between subjects 65 years of age and older and younger adult subjects.

10 OVERDOSAGE

The major risks of overdose relate predominantly to increased radiation exposure, with long-term risks for neoplasia. In the event of administration of a radiation overdose with VIZAMYL, hydration and frequent urination should be encouraged to minimize radiation exposure to the subject. It is unknown whether or not flutemetamol is dialyzable.

11 DESCRIPTION

11.1 Drug Characteristics

VIZAMYL (flutemetamol F 18 injection) is a radioactive diagnostic drug for intravenous use.

Chemically, flutemetamol F 18 is 2-[3-[^18F]fluoro-4-(methylamino) phenyl]-6-benzothiazolol. It has the molecular formula C14H11^18FN2OS, the molecular weight 273.32, and the following structural formula:

VIZAMYL is a sterile, non-pyrogenic, clear, colorless to slightly yellow solution. Each mL contains up to 2 mcg of flutemetamol and 150 MBq (4.05 mCi) of flutemetamol F 18 at reference date and time with the following inactive ingredients: 70 microL ethanol, 9 mg sodium chloride, and 4.98 mg polysorbate 80 (w/v) in 0.014 M aqueous phosphate buffer. The pH of the solution is between 6 and 8.5.

11.2 Nuclear Physical Characteristics

Fluorine-18 (F 18) decays by positron emission (ß+ decay, 96.7%) and orbital electron capture (3.3%) to stable oxygen-18 and has a physical half-life of 109.8 minutes. The principal photons useful for diagnostic imaging are the coincident pair of 511 keV gamma photons, resulting from the interaction of the emitted positron with an electron (Table 3).

Table 3: Principal Radiation Produced from Decay of Fluorine-18
Radiation | Energy Level (keV) | Abundance (%)
Positron | 249.8 | 96.7
Gamma | 511 | 193.4

The point source air-kerma rate constant for F 18 is 3.74E -17 Gy m^2/(Bq s); this coefficient was formerly defined as the specific gamma-ray constant of 5.7 R/hr/mCi at 1 cm. The first half-value thickness of lead (Pb) for F 18 gamma rays is approximately 6 mm. The relative reduction of radiation emitted by F 18 that results from various thicknesses of lead shielding is shown in Table 4. The use of ~8 cm of Pb will decrease the radiation transmission (i.e., exposure) by a factor of about 10,000.

Table 4: Radiation Attenuation of 511 keV Gamma Rays by Lead Shielding
Shield Thickness cm of Lead (Pb) | Coefficient of Attenuation
0.6 | 0.5
2 | 0.1
4 | 0.01
6 | 0.001
8 | 0.0001

For use in correcting for physical decay of this radionuclide, the fractions remaining at selected intervals after calibration are shown in Table 5.

Table 5: Physical Decay Chart for Fluorine-18
Minutes | Fraction Remaining
0 | 1.00
15 | 0.909
30 | 0.826
60 | 0.683
110 | 0.500
220 | 0.250
440 | 0.060

12 CLINICAL PHARMACOLOGY

12.1 Mechanism of Action

Flutemetamol F 18 binds to amyloid beta plaques in the brain and the F 18 isotope produces a positron signal that is detected by a PET scanner. In in vitro binding studies using postmortem human brain homogenates containing fibrillar amyloid beta, the dissociation constant (Kd) for flutemetamol was 6.7 nM.

Selectivity of ^3H-flutemetamol binding in postmortem human brain sections was demonstrated using autoradiography, silver-stained protein, and immunohistochemistry (monoclonal antibody to amyloid beta) correlation studies.

12.2 Pharmacodynamics

Following intravenous injection, flutemetamol F 18 diffuses across the human blood-brain barrier and produces a radioactivity signal detectable throughout the brain. Subsequently, cerebral perfusion decreases the brain flutemetamol F 18 content, with differential retention of the drug in cortical areas that contain amyloid beta aggregates compared to areas that lack the aggregates. The time-activity curves for flutemetamol F 18 in the brain of subjects with positive scans shows continual signal increases from time zero through 30 minutes post administration, with stable values thereafter up to at least 120 minutes post-injection. Differences in signal intensity between brain regions showing specific and non-specific flutemetamol F 18 uptake form the basis for the image interpretation method [see Dosage and Administration (2.5)].

The test-retest distribution of flutemetamol F 18 was evaluated in five subjects with probable AD who underwent two administrations of flutemetamol F 18 (followed by PET scans) separated by a time period of 1 to 4 weeks. Images were shown to maintain signal distribution reproducibility when evaluated semi-quantitatively using an automated assessment of SUVR in pre-specified cortical regions.

12.3 Pharmacokinetics

Following intravenous administration of 185 MBq (5 mCi) of VIZAMYL in healthy subjects, flutemetamol F 18 plasma concentrations declined by approximately 75% in the first 20 minutes post-injection, and by approximately 90% in the first 180 minutes. The F 18 in circulation during the 30-minute to 120-minute imaging window was principally in the form of flutemetamol metabolites. Excretion was approximately 37% renal (28% to 45%; n=6) and 52% hepatobiliary (40% to 65%; n=6).

Drug Interactions

Clinical Study

In patients with a range of cognitive impairment, mean cortical SUVR did not differ between patients taking or not taking donepezil, galantamine, memantine, or rivastigmine.

13 NONCLINICAL TOXICOLOGY

13.1 Carcinogenesis, Mutagenesis, Impairment of Fertility

Animal studies have not been performed to evaluate the carcinogenicity or reproductive toxicity potential of flutemetamol F 18.

Mutagenesis

Flutemetamol was positive for mutagenicity in two in vitro assays: the bacterial reverse mutation assay (Ames test) and the mouse lymphoma assay.

Flutemetamol was negative for genotoxicity after in vivo exposure in rats to flutemetamol at the highest cumulative dose level tested, as measured in bone marrow micronucleus assays (157 and 27 mcg/kg/day for 2 days and 14 days, respectively) and an unscheduled DNA synthesis assay in rat hepatocytes (39 mcg/kg/day).

14 CLINICAL STUDIES

14.1 Evaluation of AD and Other Causes of Cognitive Decline

The effectiveness of VIZAMYL was evaluated in two single-arm clinical studies (i.e., Studies 1 and 2) in adult subjects with a range of cognitive function, including some terminally ill subjects who had agreed to participate in a postmortem brain donation program as well as healthy subjects. Subjects underwent a VIZAMYL injection and scan. The images were interpreted using a clinically applicable binary image interpretation method (negative or positive) by five independent readers blinded to all clinical information [see Dosage and Administration (2.3, 2.4, 2.5)]. PET images were reviewed first without, and subsequently with, brain CT or MRI images. Before image interpretation, all readers underwent in-person training or electronic media training.

To determine the agreement between the in vivo VIZAMYL image results and the postmortem amyloid beta neuritic plaque density, VIZAMYL results (negative or positive) were pre-specified to correspond with specific histopathology-derived plaque density scores, based upon a modification of the Consortium to Establish a Registry for Alzheimer's Disease (CERAD) criteria (Table 6), which use neuritic plaque counts as a necessary pathological feature of AD. Plaques were counted on microscope slides with modified Bielschowsky silver stained tissue sections. The global neuritic plaque density score for each subject was determined by averaging across the scores (0-3) for five gray matter fields per slide and then across six slides for each of eight regions; if any one region had a score of greater than 1.5, the subject was classified as positive for amyloid beta.

Table 6: Categorization of Histopathology and VIZAMYL PET Read
Histopathology Categorization |  | VIZAMYL PET Read
Neuritic Plaque Counts | CERAD Score | VIZAMYL PET Read
0 | None (0) | Negative
1 to 5 | Sparse (1) | Negative
6 to 19 | Moderate (2) | Positive
>20 | Frequent (3) | Positive

Study 1 evaluated performance characteristics (sensitivity and specificity) in terminally ill subjects by comparing the premortem VIZAMYL PET images to a postmortem truth standard of cortical amyloid beta neuritic plaque density. A total of 180 subjects were dosed with VIZAMYL and 176 were imaged. The mean age was 80 years (range 47 to 98 years) and 57% of the subjects were female. By medical history, 135 subjects had dementia, one subject had memory loss of unspecified nature, and 44 subjects had no cognitive impairment. Among the imaged subjects, 68 subjects who died during the study and had cerebral cortical amyloid status determined were included in the primary analysis. The time interval between the VIZAMYL scan and death ranged from 0 to 13 months, with a median of 2.6 months, and was less than one year for 66 subjects and between 12 to 13 months for 2 subjects. At autopsy, the global brain neuritic plaque density category (CERAD score as in Table 6) was available for 67/68 subjects: frequent (n = 19); moderate (n = 22); sparse (n = 14); and none (n = 12).

Study 2 evaluated inter-reader and intra-reader reproducibility of image interpretation using images from subjects with a truth standard (68 subjects who underwent an autopsy in Study 1 and 36 subjects who had known or suspected normal pressure hydrocephalus with in vivo brain biopsy) and subjects without a truth standard (80 subjects with amnestic mild cognitive impairment (aMCI), 33 subjects with probable AD (pAD), 28 cognitively normal subjects 55 years of age and older, and 31 young healthy subjects). Additionally, intra-reader reproducibility was assessed with images from 29 subjects (10%). Among the 276 subjects, the mean age was 68 years (range 20 to 95 years), 136 were females, and 251 were White. Readers were naïve to all forms of amyloid PET imaging and underwent electronic media training.

Among subjects who underwent autopsy (n=68; 43 positive and 25 negative based on histopathology), the sensitivity using the majority interpretation of the readers trained using electronic media was 93% (95% CI: 81%, 99%) and specificity was 84% (95% CI: 64%, 96%). The median (and range) of correct, false negative, and false positive reads were 59 (51, 61), 5 (3, 8), 3 (2, 14), respectively, for in-person training; and were 60 (55 to 61), 3 (3 to 6), 4 (2 to 10), respectively, for electronic media training.

Table 7 shows inter-reader reproducibility results among readers for various subject groups in Study 2. Inter-reader reproducibility analyses showed an overall Fleiss' kappa statistic of 0.83 (95% CI: 0.79, 0.86), which met the pre-specified success criterion (95% CI lower bound > 0.60). Intra-reader reproducibility analyses showed that between the two readings for each of the 29 duplicate scans, one of the five readers had complete agreement for all 29 scans, two readers had discordant reads for a single scan, and two readers had discordant reads for two scans. Intra-reader reproducibility for a subgroup of eight scans from aMCI subjects showed that all five readers had complete agreement for all duplicate scans.

Table 7: Inter-Reader Reproducibility of VIZAMYL PET Read Results for Various Subject Groups in Study 2 [Readers were naïve to all forms of amyloid PET imaging and underwent electronic media training.]
Subject Group by Cognitive Status and Truth Standard (TS) | Positive Scans, N [Shown is the median number of scans interpreted as positive across the five readers for each subgroup of subjects listed in the first column.] | Kappa (95% CI) | Percent of Scans with Inter-Reader Agreement
Subject Group by Cognitive Status and Truth Standard (TS) | Positive Scans, N [Shown is the median number of scans interpreted as positive across the five readers for each subgroup of subjects listed in the first column.] | Kappa (95% CI) | 3 of 5 readers agreed | 4 of 5 readers agreed | 5 of 5 readers agreed
All subjects, n=276 | 139 | 0.83 (0.79, 0.86) | 5 | 14 | 81
All subjects with TS, n=104 (68 autopsy; 36 biopsy) | 58 | 0.74 (0.68, 0.80) | 6 | 24 | 70
All subjects without TS, n=172 | 76 | 0.88 (0.83, 0.92) | 5 | 8 | 87
pAD, n=63 (30 autopsy; 33 no TS) | 47 | 0.88 (0.80, 0.96) | 3 | 6 | 90
aMCI without TS, n=80 | 45 | 0.89 (0.82, 0.96) | 4 | 7 | 89
Other non-AD dementia with TS, n=53 (17 autopsy; 36 biopsy [5 of 36 subjects with TS from biopsy were not definitively classified as pAD based on clinical diagnosis]) | 27 | 0.71 (0.63, 0.80) | 8 | 25 | 68
Cognitively normal with TS, n=21 (21 autopsy) | 10 | 0.64 (0.5, 0.77) | 5 | 38 | 57
Cognitively normal 55 years of age and older without TS, n=28 | 2 | 0.46 (0.34, 0.57) | 4 | 14 | 82
pAD: probable AD; aMCI: amnestic MCI

14.2 Selection of Patients Indicated for Amyloid Beta-Directed Therapy

Refer to the prescribing information of the amyloid beta-directed therapy for description of clinical trials in which the efficacy of amyloid beta PET for selecting patients has been established.

Brain amyloid beta PET scans have been used to assess reduction of plaque in some clinical trials of amyloid beta-directed therapies as also described in the prescribing information of the therapeutic products.

16 HOW SUPPLIED/STORAGE AND HANDLING

How Supplied

VIZAMYL (flutemetamol F 18 injection) is a clear, colorless to slightly yellow solution supplied at a concentration of 150 MBq/mL (4.05 mCi/mL) of flutemetamol F 18 in up to 30 mL volume at reference date and time in a shielded multiple-dose glass vial (NDC 17156-067-30).

Storage and Handling

Store VIZAMYL in the original container within radiation shielding at 2°C to 30°C (36°F to 86°F).

VIZAMYL does not contain a preservative.

Do not use after the expiry date and time stated on the label. VIZAMYL multiple-dose vial expires 10 hours after end of synthesis (EOS).

Dispose of any unused product in accordance with all federal, state, and local laws and institutional requirements.

This preparation is for use by persons licensed by the Nuclear Regulatory Commission or the relevant regulatory authority of an Agreement State.

17 PATIENT COUNSELING INFORMATION

Anaphylaxis and Other Serious Hypersensitivity Reactions

Inform patients of the risk of hypersensitivity reactions, including anaphylaxis, and instruct them to alert healthcare providers immediately if they experience signs and symptoms of a hypersensitivity reaction [see Warnings and Precautions (5.1)].

Radiation Risk

Advise patients of the radiation risk of VIZAMYL. Instruct patients to increase their level of hydration before and after receiving VIZAMYL and to void frequently following administration [see Warnings and Precautions (5.3)].

Pregnancy

Inform pregnant women of the potential risks of fetal exposure to radiation doses with VIZAMYL [see Use in Specific Populations (8.1)].

Lactation

Advise a lactating woman to temporarily discontinue breastfeeding and to pump and discard breast milk for 24 hours after VIZAMYL administration to minimize radiation exposure to the breastfed infant [see Use in Specific Populations (8.2)].

Manufactured for
GE Healthcare, Medi-Physics, Inc.
Arlington Heights, IL 60004
U.S.A.

VIZAMYL is a trademark of GE HealthCare or one of its subsidiaries.
GE is a trademark of General Electric Company used under trademark license.

© 2025 GE HealthCare

PRINCIPAL DISPLAY PANEL - 30 mL Vial Label

NDC 17156-067-30

Multiple-Dose Vial
Sterile, Non-Pyrogenic
Rx ONLY

CAUTION
RADIOACTIVE
MATERIAL

Vizamyl™
(flutemetamol F 18 injection)
150 MBq/mL (4.05 mCi/mL) at reference date and time
Diagnostic - For Intravenous Use Only.

Batch No.: ___________________ Date: ______________________Vial No.:_______________
Each mL contains up to 2 micrograms of flutemetamol and 150 MBq (4.05 mCi) flutemetamol F
18 at reference date and time, 70 microL ethanol, 9 mg sodium chloride, and 4.98 mg
polysorbate 80 (w/v) in 0.014 M aqueous phosphate buffer.
Store at 2°C to 30°C (36°F to 86°F). Recommended dosage: See prescribing information.

Distributed by GE HealthCare, Medi-Physics Inc., Arlington Heights, IL 60004, U.S.A.

40-3067A

PRINCIPAL DISPLAY PANEL - 30 mL Vial Container Label

NDC 17156-067-30

Multiple-Dose Vial
Sterile, Non-Pyrogenic
Rx ONLY

CAUTION
RADIOACTIVE
MATERIAL

Vizamyl™
(flutemetamol F 18 injection)
150 MBq/mL (4.05 mCi/mL) at reference date and time

_______ MBq (________ mCi) in ________ mL at ______:______on _______________

Batch No.: _______________________ Date: ___________________ Vial No.: _______

Diagnostic - For Intravenous Use Only.

Recommended dosage: See prescribing information.

Contents per mL of Vizamyl (flutemetamol F 18 injection) solution at
reference time: ____________________ , up to 2 micrograms of
flutemetamol and 150 MBq (4.05 mCi) flutemetamol F 18, 70 microL
ethanol, 9 mg sodium chloride, and 4.98 mg polysorbate 80 (w/v) in 0.014
M aqueous phosphate buffer. Store at 2°C to 30°C (36°F to 86°F).

Expires at ______:______ on _________________

Distributed by GE HealthCare, Medi-Physics Inc., Arlington Heights, IL 60004, U.S.A.

41-3067A